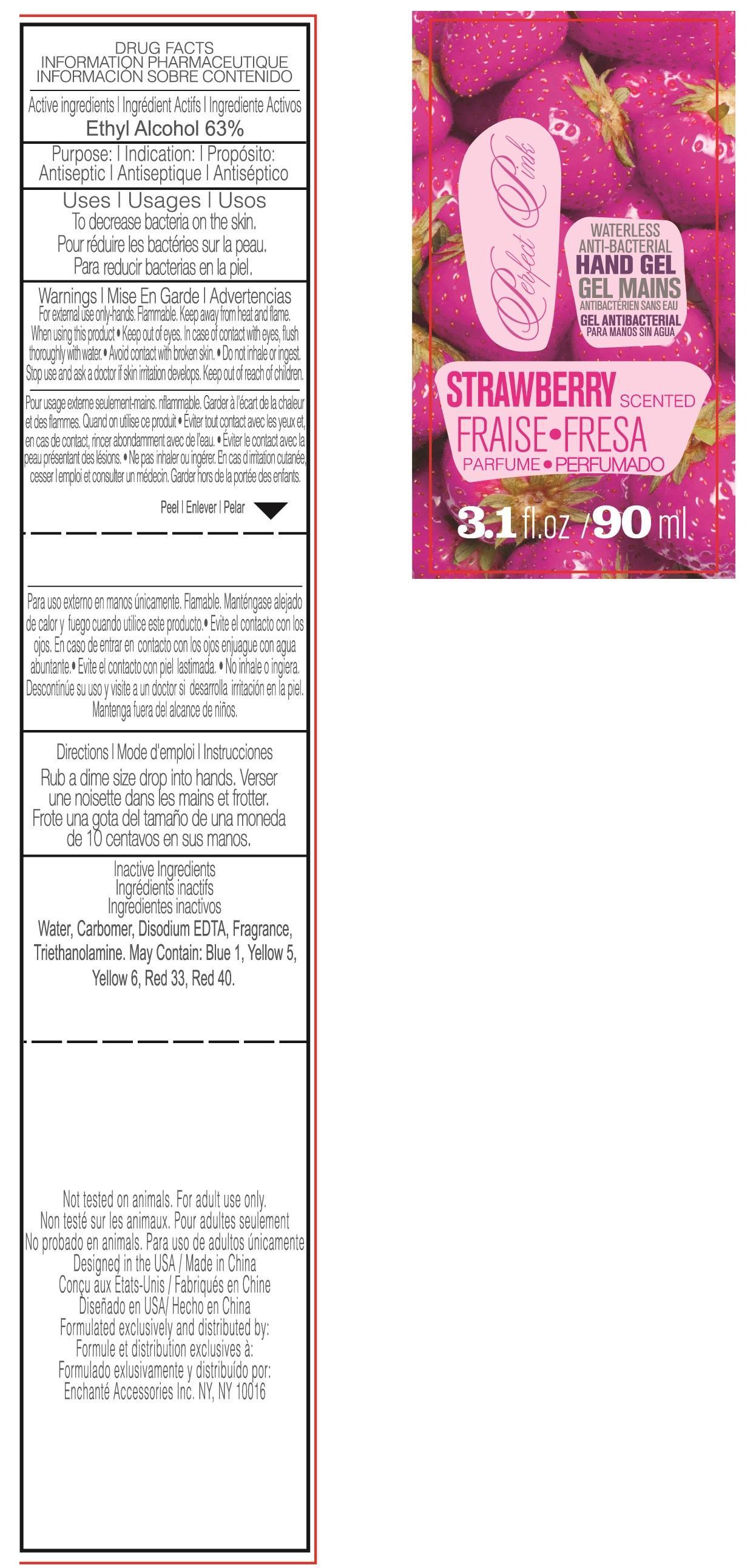 DRUG LABEL: Body Luxuries Strawberry Scented Waterless Anti Bacterial Hand gel
NDC: 50563-147 | Form: LIQUID
Manufacturer: ENCHANTE ACCESSORIES INC. 
Category: otc | Type: HUMAN OTC DRUG LABEL
Date: 20130906

ACTIVE INGREDIENTS: ALCOHOL 63 mL/100 mL
INACTIVE INGREDIENTS: WATER 33.8 mL/100 mL; CARBOMER COPOLYMER TYPE A; TROLAMINE; EDETATE DISODIUM; D&C RED NO. 33; FD&C BLUE NO. 1; FD&C YELLOW NO. 5; FD&C YELLOW NO. 6; FD&C RED NO. 40

Drug Fact

Active Ingredient

Ethyl Alcohol 63%

Purpose

Antiseptic

Uses

To decrease bacteria on the skin

WARNINGS

For external use only, hands. Flammable, keep away from heat and flame.

When using this product: Keep out of eyes. In case of contact with eyes, flush throughly with water.

Avoid contact with broken skin. Do not inhale or ingest.

Stop use and ask a doctor if skin irritation develops

Keep out of reach of children.

Directions

- Rub a dime size drop into hands

Inactive Ingredient:

Aqua, Carbomer, Triethanolamine, Parfum, Disodium EDTA, may contain D and C Red No. 33, FD and C Red No. 40, FD and C Blue No. 1, FD and C Yellow No. 5, FD and C Yellow No. 6.

PACKAGE LABEL

lab